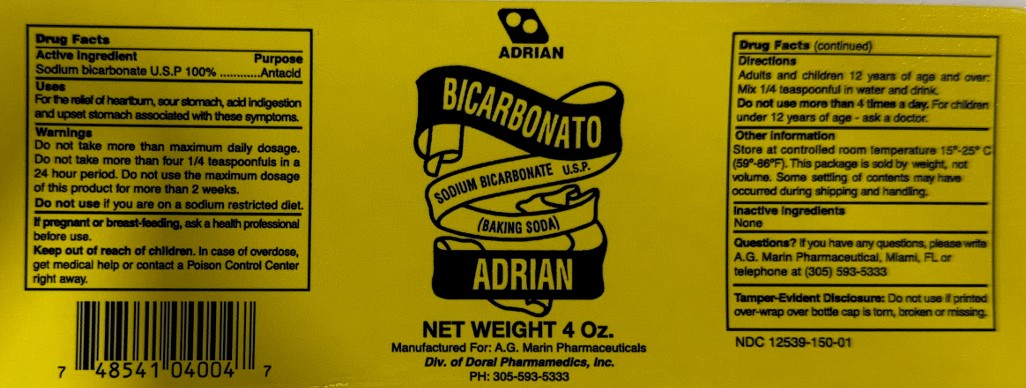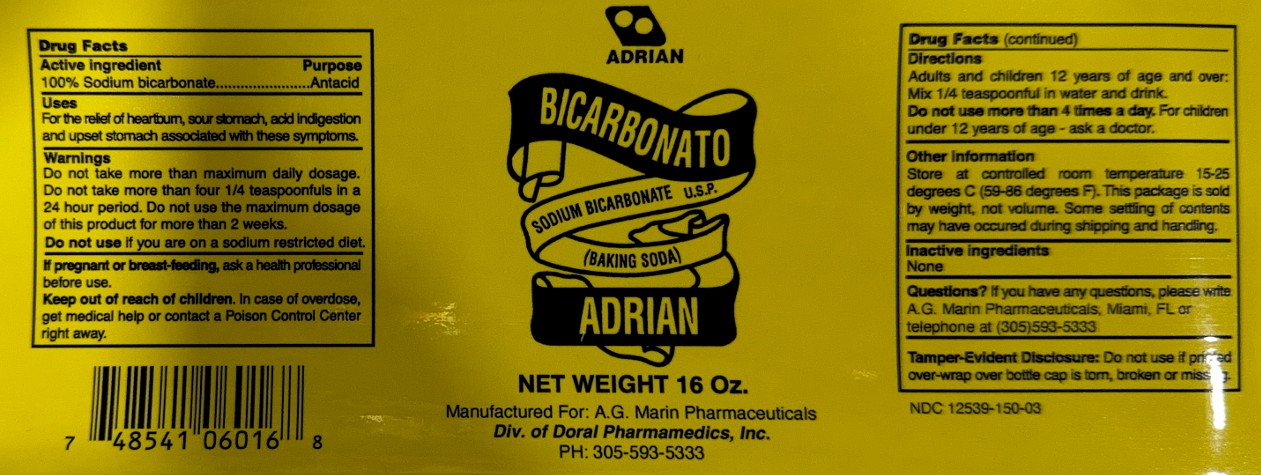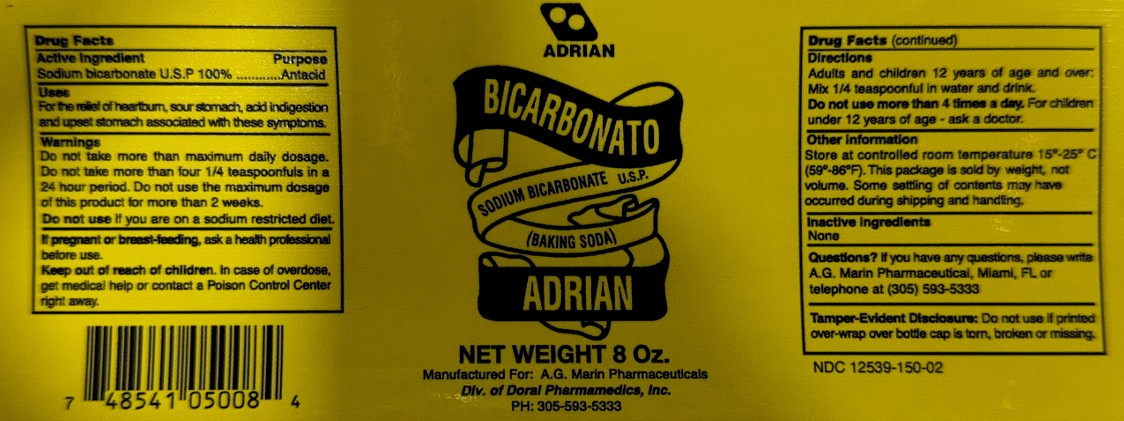 DRUG LABEL: ADRIAN BICARBONATO
NDC: 84178-106 | Form: POWDER
Manufacturer: Evi Labs
Category: otc | Type: HUMAN OTC DRUG LABEL
Date: 20260128

ACTIVE INGREDIENTS: SODIUM BICARBONATE 315 mg/1 g

ADRIAN BICARBONATO

Active Ingredients

Sodium bicarbonate USP 100%

Purpose

Antacid

Uses

For the relief of heartburn, sour stomach, acid indigestion, and upset stomach associated with these symptoms.

Warnings

Do not take more than the maximum daily dosage. Do not take more than four 1/4 teaspoonfuls in 24 hours. Do not use the maximum dosage of this product for more than 2 weeks. Do not use if you are on a sodium-restricted diet.

If pregnant or breastfeeding, ask a health professional before use.

Keep out of reach of children. In case of overdose, get medical help or contact a Poison Control Center right away.

Directions

Adults and children 12 years of age and over: Mix 1/4 teaspoonful in water and drink. Do not use more than 4 times a day. For children under 12 years of age- ask a doctor.

Other Information

Storage at controlled room temperature 15º-25º C (59ºF-89ºF). This package is sold by weight, not volume. Some settings of contents may have occurred during shipping and handling.

Inactive Ingredients

none

Tamper-Evident Disclosure

Do not use if printed over-wrap over the bottle cap is torn, broken, or missing.